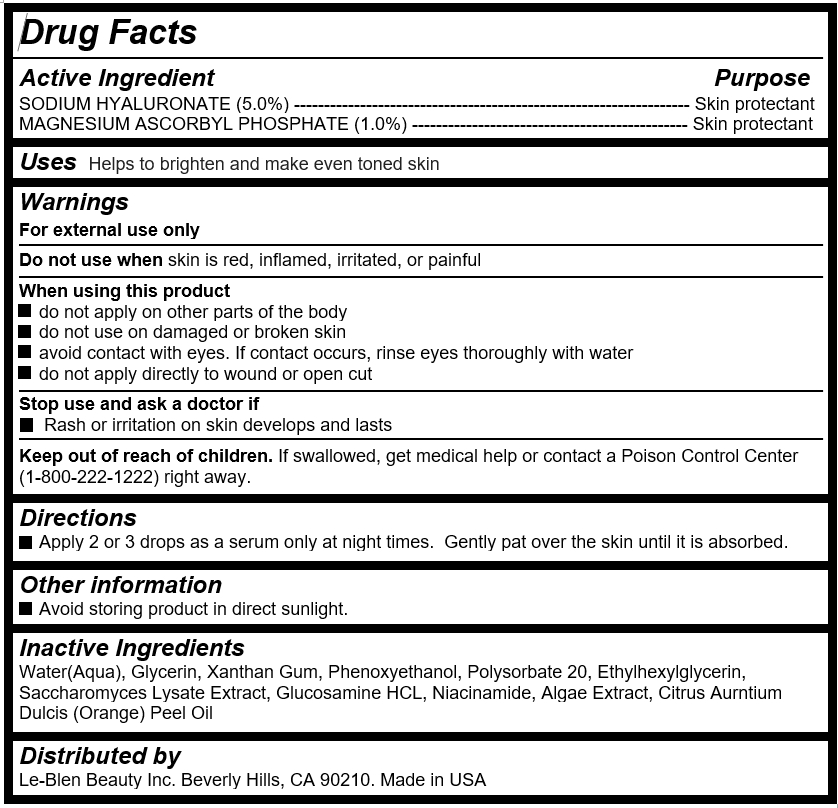 DRUG LABEL: Le-Blen Vitamin C Serum
NDC: 72271-103 | Form: LOTION
Manufacturer: LeBlen Beauty Inc
Category: otc | Type: HUMAN OTC DRUG LABEL
Date: 20180430

ACTIVE INGREDIENTS: MAGNESIUM ASCORBYL PHOSPHATE 0.57 g/56.7 g; HYALURONATE SODIUM 2.84 g/56.7 g
INACTIVE INGREDIENTS: WATER

Le-Blen Vitamin C Serum

Active Ingredients

SODIUM HYALURONATE (5.0%) ------------------------------------------------------------------ Skin protectant

MAGNESIUM ASCORBYL PHOSPHATE (1.0%) ---------------------------------------------- Skin protectant

Purposes

Skin Protectant

Uses

Helps to brighten and make even toned skin

Keep out of reach of children

If swallowed, get medical help or contact a Poison Control Center (1-800-222-1222) right away.

Directions

Apply 2 or 3 drops after cleansing. Massage gently until it is absorbed.

Warnings

For external use only

Do not use when skin is red, inflamed, irritated, or painful

When using this product

do not apply on other parts of the body

do not use on damaged or broken skin

avoid contact with eyes. If contact occurs, rinse eyes thoroughly with water

do not apply directly to wound or open cut

Stop use and ask a doctor if

Rash or irritation on skin develops and lasts

Inactive Ingredients

Water(Aqua), Glycerin, Xanthan Gum, Phenoxyethanol, Polysorbate 20, Ethylhexylglycerin, Saccharomyces Lysate Extract, Glucosamine HCL, Niacinamide, Algae Extract, Citrus Aurntium Dulcis (Orange) Peel Oil